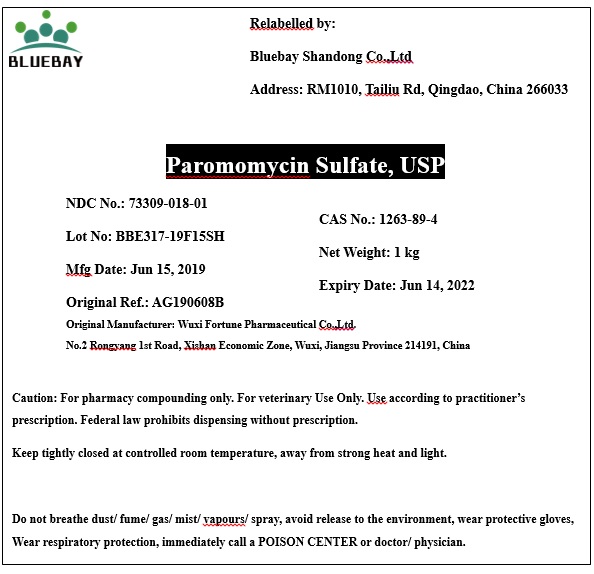 DRUG LABEL: Paromomycin Sulfate
NDC: 73309-018 | Form: POWDER
Manufacturer: BLUEBAY SHANDONG CO.,LTD
Category: other | Type: BULK INGREDIENT
Date: 20190821

ACTIVE INGREDIENTS: PAROMOMYCIN SULFATE 1 kg/1 kg

Paromomycin Sulfate